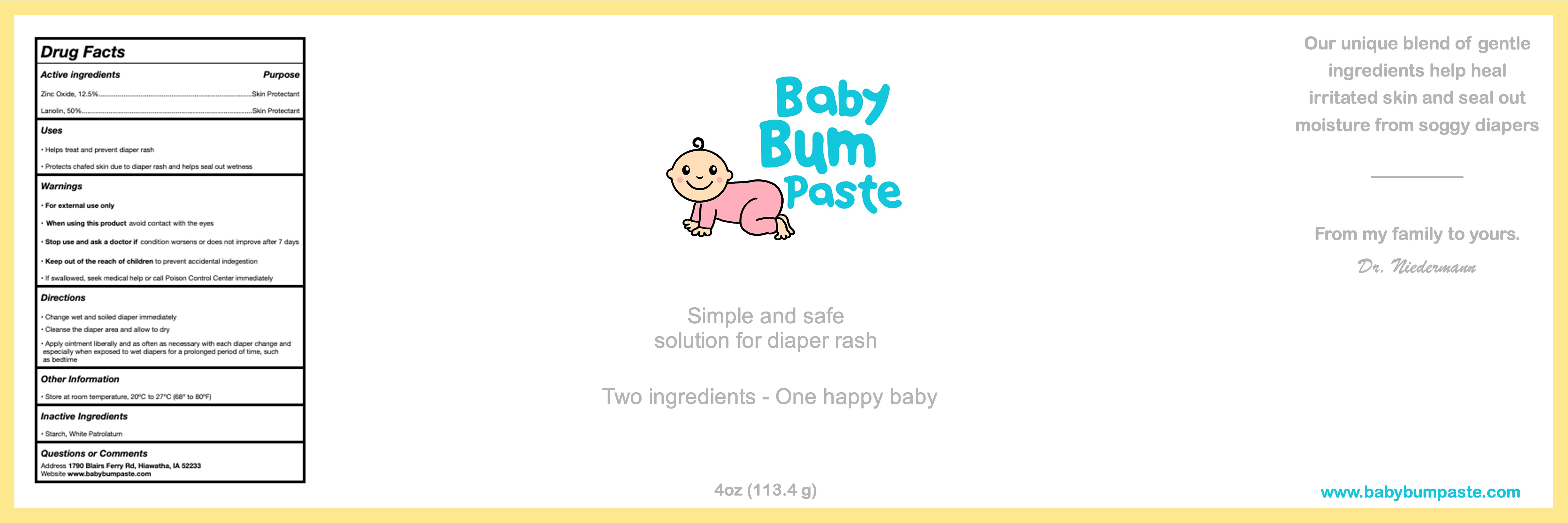 DRUG LABEL: Baby Bum
NDC: 72997-808 | Form: PASTE
Manufacturer: Blairs Ferry Pharmacy
Category: otc | Type: HUMAN OTC DRUG LABEL
Date: 20191218

ACTIVE INGREDIENTS: ZINC OXIDE 0.125 g/1 g; LANOLIN 0.5 g/1 g
INACTIVE INGREDIENTS: STARCH, CORN; PETROLATUM

Baby Bum Paste

Active ingredients

Zinc Oxide 12.5%

Lanolin USP 50%

Uses

- Helps treat and prevent diaper rash
- Protects chafed skin due to diaper rash and helps seal out wetness

Purpose

Skin Protectant

Skin Protectant

Warnings

- For external use only
- When using this product avoid contact with eyes
- Stop use and ask a doctor if conditions worsens or does not improve after 7 days
- If swallowed, seek medical help or call Poison Control Center immediately

KEEP OUT OF REACH OF CHILDREN

- Keep out of the reach of children to prevent accidental indigestion

Directions

- Change wet or soiled diaper immediately
- Cleanse the diaper area and allow to dry
- Apply ointment liberally and as often as necessary with each diaper change and especially when exposed to wet diapers for a prolonged period of time, such as bedtime

Other Information

- Store at room temperature, 20°C to 27°C (68° to 80°F)

Inactive Ingredients

- Starch, White Petrolatum

Questions or Comments

Address 1790 Blairs Ferry Rd, Hiawatha, IA 52233

Website www.babybumpaste.com